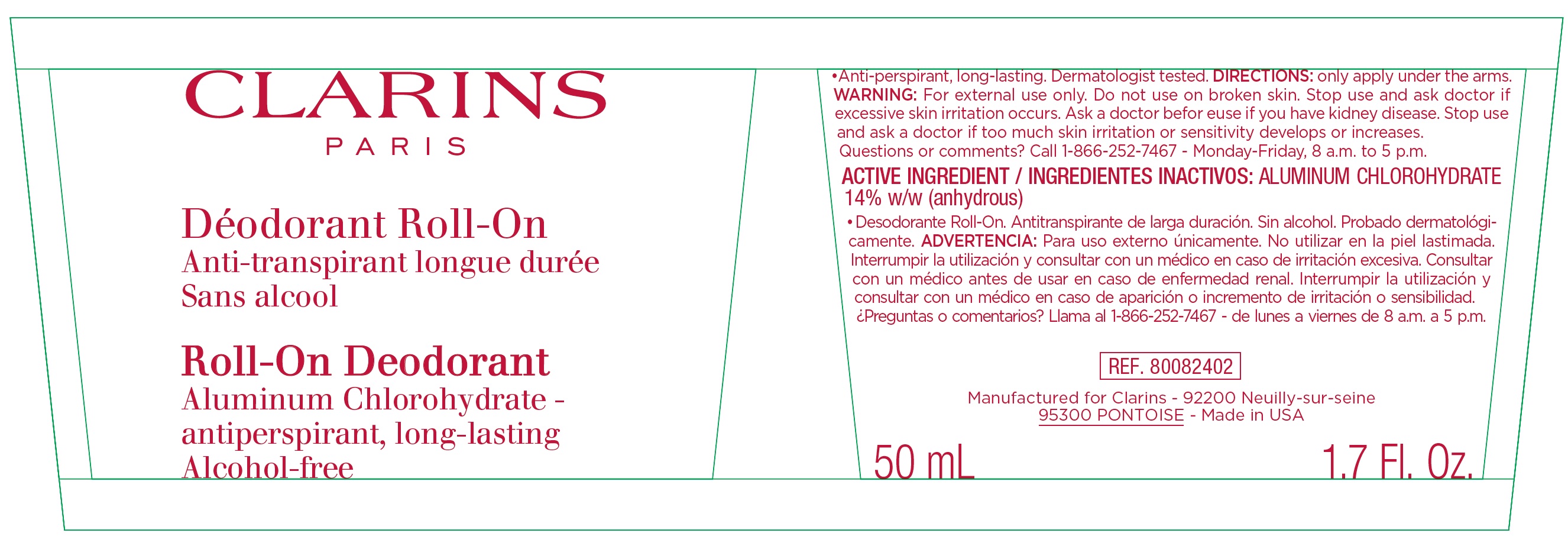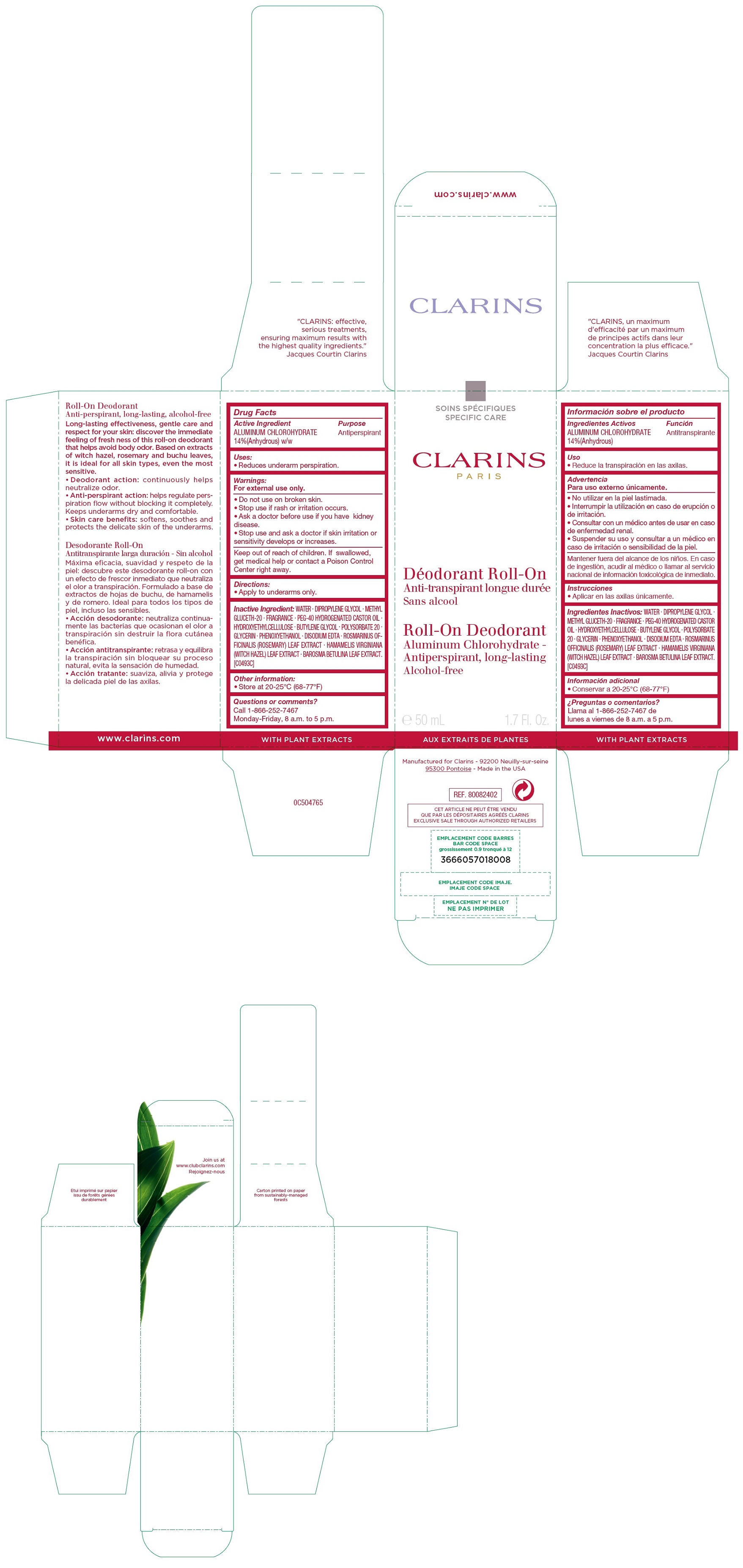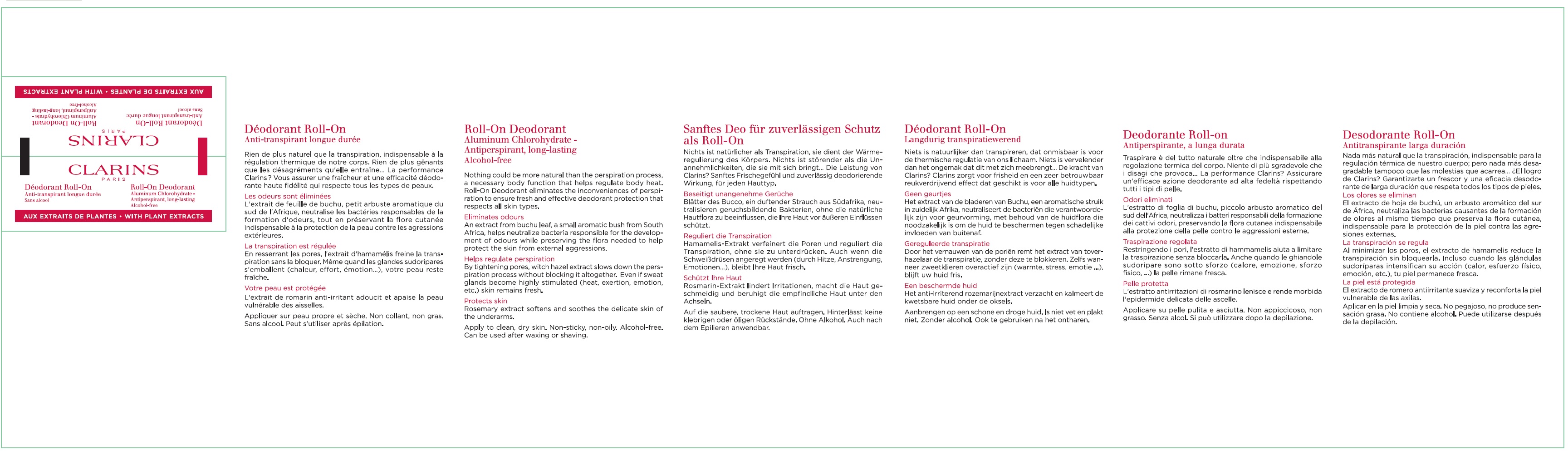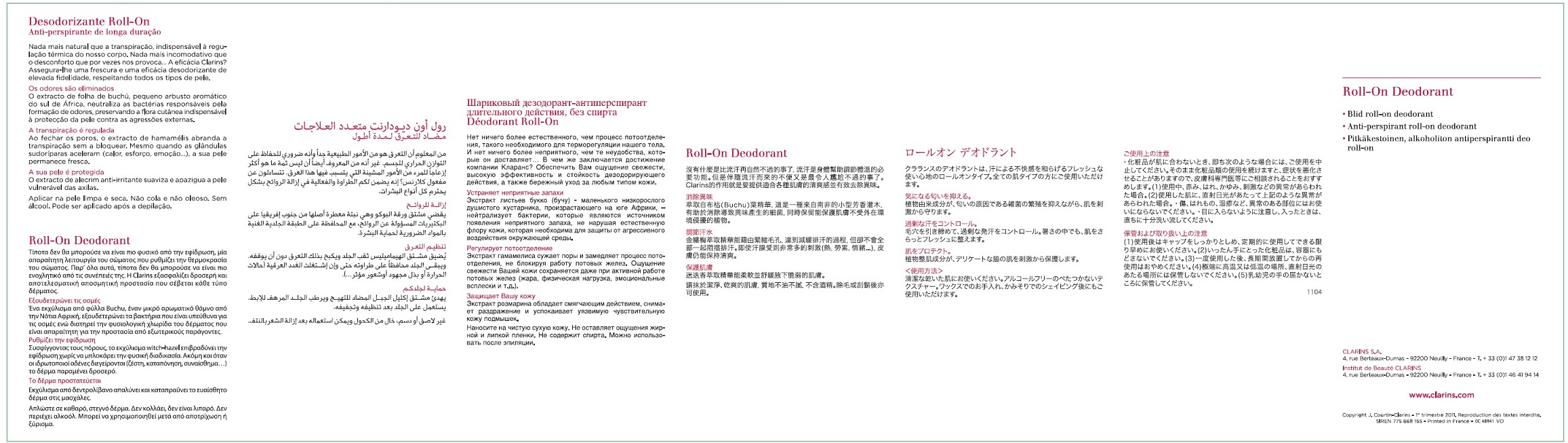 DRUG LABEL: CLARINS - ROLL-ON DEODORANT Aluminum Chlorohydrate - Antiperspirant, long-lasting, Alcohol-free
NDC: 58668-5971 | Form: LIQUID
Manufacturer: Laboratoires Clarins
Category: otc | Type: HUMAN OTC DRUG LABEL
Date: 20231214

ACTIVE INGREDIENTS: ALUMINUM CHLOROHYDRATE 140 mg/1 mL
INACTIVE INGREDIENTS: WATER; DIPROPYLENE GLYCOL; METHYL GLUCETH-20; POLYOXYL 40 HYDROGENATED CASTOR OIL; HYDROXYETHYL CELLULOSE, UNSPECIFIED; BUTYLENE GLYCOL; POLYSORBATE 20; GLYCERIN; PHENOXYETHANOL; EDETATE DISODIUM ANHYDROUS; ROSEMARY; HAMAMELIS VIRGINIANA LEAF; AGATHOSMA BETULINA LEAF

CLARINS - ROLL-ON DEODORANT Aluminum Chlorohydrate - Antiperspirant, long-lasting, Alcohol-free

Active Ingredient

ALUMINUM CHLOROHYDRATE 14%(Anhydrous) w/w

Purpose

Antiperspirant

Uses:

• Reduces underarm perspiration.

: Warnings

For external use only.

Do not use

- on broken skin.
- Stop use if rash or irritation occurs

Ask a doctor before use

- if you have kidney disease.

Stop use and ask a doctor

- if skin irritation or sensitivity develops or increases.

Keep out of reach of children.

If swallowed, get medical help or contact a Poison Control Center right away.

Directions:

• Apply to underarms only.

Inactive Ingredient:

WATER . DIPROPYLENE GLYCOL . METHYL GLUCETH-20 . FRAGRANCE . PEG-40 HYDROGENATED CASTOR OIL . HYDROXYETHYLCELLULOSE . BUTYLENE GLYCOL . POLYSORBATE 20 . GLYCERIN . PHENOXYETHANOL . DISODIUM EDTA . ROSMARINUS OFFICINALIS (ROSEMARY) LEAF EXTRACT . HAMAMELIS VIRGINIANA (WITCH HAZEL) LEAF EXTRACT . BAROSMA BETULINA LEAF EXTRACT. [C0493C]

Other information:

• Store at 20-25°C (68-77°F)

Questions or comments?

Call 1-866-252-7467 Monday-Friday, 8 a.m. to 5 p.m.